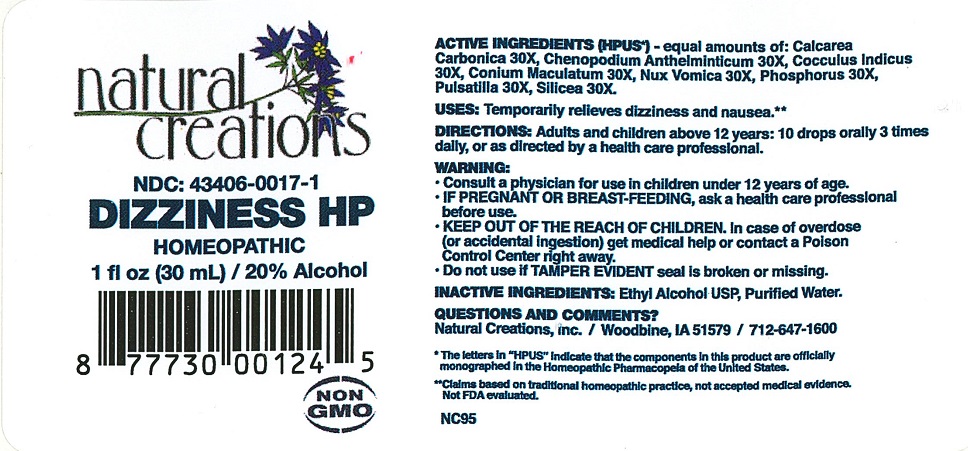 DRUG LABEL: DIZZINESS HP
NDC: 43406-0017 | Form: LIQUID
Manufacturer: Natural Creations, Inc.
Category: homeopathic | Type: HUMAN OTC DRUG LABEL
Date: 20251210

ACTIVE INGREDIENTS: OYSTER SHELL CALCIUM CARBONATE, CRUDE 30 [hp_X]/1 mL; CHENOPODIUM AMBROSIOIDES 30 [hp_X]/1 mL; ANAMIRTA COCCULUS SEED 30 [hp_X]/1 mL; CONIUM MACULATUM FLOWERING TOP 30 [hp_X]/1 mL; STRYCHNOS NUX-VOMICA SEED 30 [hp_X]/1 mL; PHOSPHORUS 30 [hp_X]/1 mL; PULSATILLA VULGARIS 30 [hp_X]/1 mL; SILICON DIOXIDE 30 [hp_X]/1 mL
INACTIVE INGREDIENTS: WATER; ALCOHOL

DIZZINESS HP

ACTIVE INGREDIENT

ACTIVE INGREDIENTS (HPUS*) - equal amounts of: Calcarea Carbonica 30X, Cheopodium Anthelminticum 30X, Cocculus Indicus 30X, Conium Maculatum 30X, Nux Vomica 30X, Phosphorus 30X, Pulsatilla 30X, Silicea 30X

PURPOSE

USES: Temporarily relieves dizziness and nausea.**

INDICATIONS AND USAGE

USES: Temporarily relieves dizziness and nausea.**

DOSAGE AND ADMINISTRATION

Directions: Adults & children above 12 years: 10 drops orally 3 times daily, or as directed by a health care professional.

KEEP OUT OF REACH OF CHILDREN

KEEP OUT OF THE REACH OF CHILDREN. In case of overdose (or accidental ingestion) get medical help or contact a Poison Control Center right away

WARNINGS:

- Consult a physician for use in children under 12 years of age.
- IF PREGNANT OR BREAST-FEEDING, ask a health care professional before use.
- KEEP OUT OF THE REACH OF CHILDREN. In case of overdose (or accidental ingestion) get medical help or contact a Poison Control Center right away.
- Do not use if TAMPER EVIDENT seal is broken or missing.

Inactive Ingredients: Purified Water, USP Ethanol Alcohol 20%

QUESTIONS

Questions & Comments? Natural Creations, Inc. / Woodbine, IA 51579 / 712-647-1600

REFERENCES

*The letters “HPUS” indicate the components in the product are officially monographed in the Homeopathic Pharmacopeia of the United States.

**Claims based on traditional homeopathic practice, not accepted medical evidence. Not FDA evaluated.

PACKAGE LABEL

NDC: 43406-0017-1

DIZZINESS HP

HOMEOPATHIC

1 fl oz (30 mL) 20% Alcohol